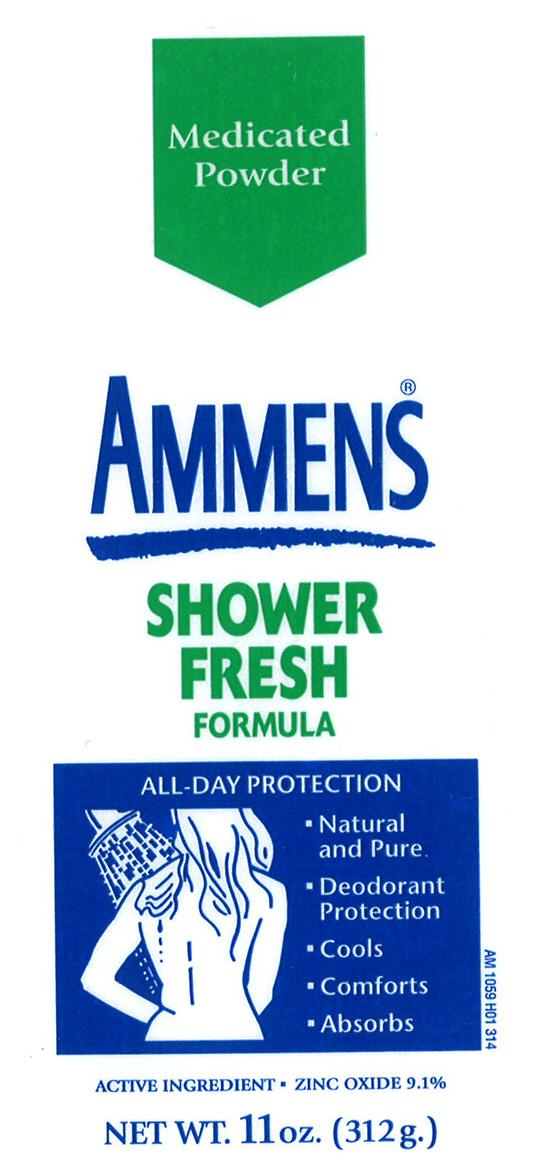 DRUG LABEL: Ammens Medicated Powder Shower Fresh Formula
NDC: 41595-1059 | Form: POWDER
Manufacturer: Idelle Labs, Ltd
Category: otc | Type: HUMAN OTC DRUG LABEL
Date: 20130521

ACTIVE INGREDIENTS: ZINC OXIDE 9.1 g/100 g
INACTIVE INGREDIENTS: STARCH, CORN; ISOSTEARIC ACID; TALC

Ammens Medicated Powder Shower Fresh Formula

Medicated Powder
Ammens
Shower Fresh Formula

All-Day Protection

- Natural and Pure
- Deodorant Protection
- Cools
- Comforts
- Absorbs

Active Ingredient Zinc Oxide 9.1%
MM1

Active Ingredient:

Zinc Oxide 9.1%

Purpose:

Skin protectant powder

Uses:

Dries the oozing and weeping of poison

- ivy
- oak
- sumac

Warning:

For external use only.

When using this product

do not get into eyes.

Stop use and ask a doctor if

- condition worsens
- symptoms last more than 7 days or clear up and occur again within a few days

Keep out of reach of children.

If swallowed, get medical help or contact a Poison Control Center right away.

Directions:

Apply as needed.

Other Information:

- Do not use on broken skin.
- When using this product, keep away from face and mouth to avoid breathing it in.

Inactive Ingredients:

Corn starch, fragrance, isostearic acid, PPG-20 methyl glucose ether, talc.

Questions or comments?

1-800-487-7273

©2004 Idelle Labs, Ltd. All rights reserved
Made in the USA and distributed by Idelle Labs, Ltd., El Paso, TX 79912

label